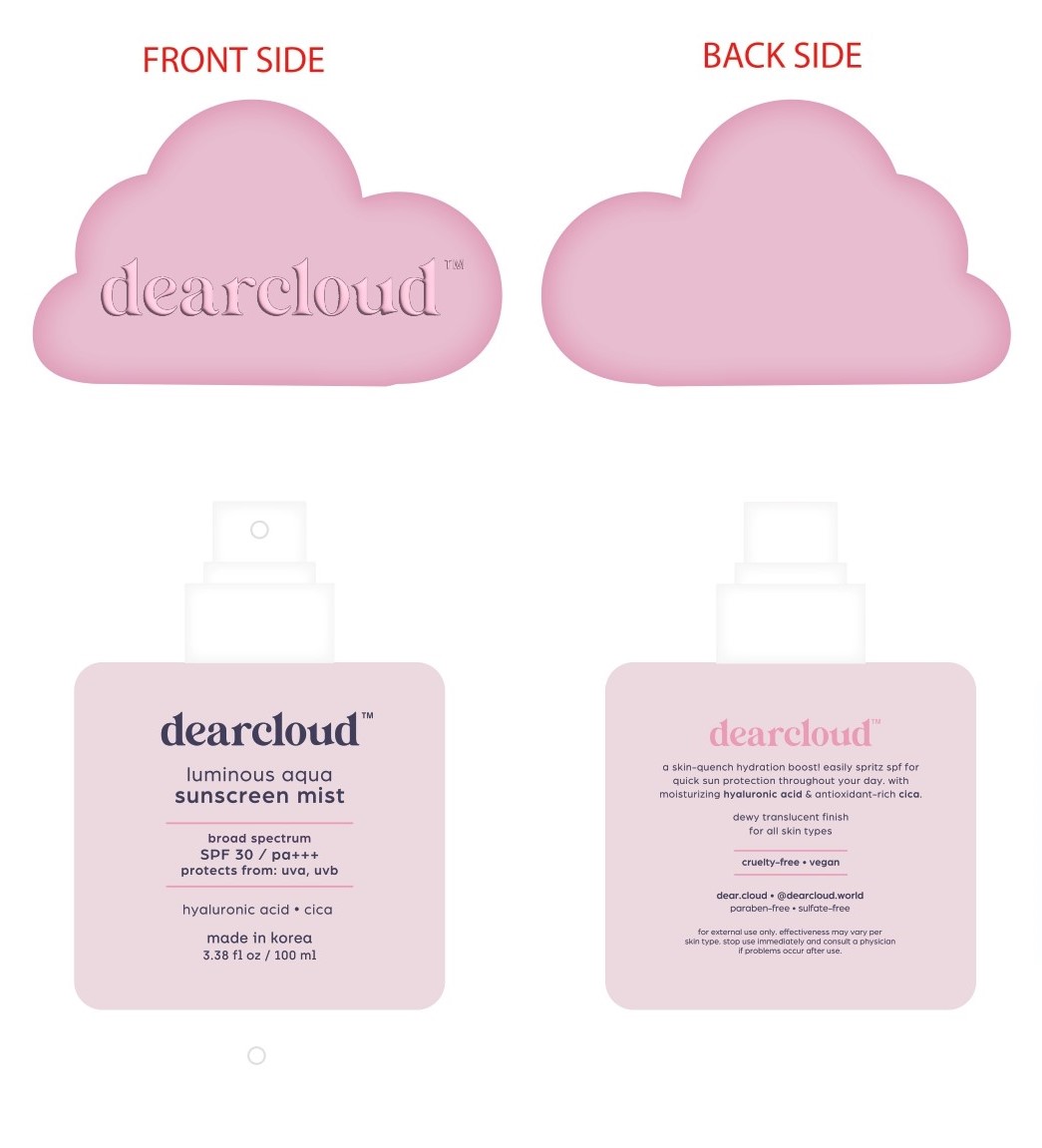 DRUG LABEL: luminous aqua sunscreen mist
NDC: 84326-724 | Form: SPRAY
Manufacturer: RBGROUP Co., Ltd
Category: otc | Type: HUMAN OTC DRUG LABEL
Date: 20251021

ACTIVE INGREDIENTS: OCTOCRYLENE 9.5 g/100 g; AVOBENZONE 2.8 g/100 g; OCTISALATE 4.8 g/100 g; HOMOSALATE 7.3 g/100 g
INACTIVE INGREDIENTS: MADECASSIC ACID; ALCOHOL; BENZYL GLYCOL; ETHYLHEXYLGLYCERIN; ETHYL HEXANEDIOL; ASIATICOSIDE; ASIATIC ACID; SODIUM ACETYLATED HYALURONATE; HYALURONIC ACID; BUTYLOCTYL SALICYLATE; BUTYLENE GLYCOL; WATER; 1,2-HEXANEDIOL; SODIUM HYALURONATE; ISOPROPYL MYRISTATE; ACRYLATES/OCTYLACRYLAMIDE COPOLYMER (40000 MW); GLYCERIN

84326-724 luminous aqua sunscreen mist

ACTIVE INGREDIENT

Avobenzone 2.5%

Homosalate 9.5%

Octisalate 4.5%

Octocrylene 9.5%

PURPOSE

Sunscreen

INDICATIONS AND USAGE

● Helps prevent sunburn.

● If used as directed with other sun protection measures (see Directions), decreases the risk of skin cancer and early skin aging caused by the sun.

WARNINGS

For external use only

DO NOT USE

● on damaged or broken skin

WHEN USING

this product ● keep out of eyes. Rinse with water to remove.

KEEP OUT OF REACH OF CHILDREN

If swallowed, get medical help or contact a Poison Control Center right away.

STOP USE

and ask a doctor if rash occurs.

Directions

● Spray liberally and spread evenly by hand 15 minutes before sun exposure.

● Apply to all skin exposed to the sun.

● Do not spray directly into face.

● Spray on hands and then apply to face. Rub in.

● If bothersome dryness or peeling occurs, reduce application to once a day or every other day.

● Do not apply in windy conditions.

● Reapply at least every 2 hours.

● Children under 6 months of age: Ask a doctor

● Sun Protection Measures. Spending time in the sun increases your risk of skin cancer and early skin aging. ● To decrease this risk, regularly use a sunscreen with a Broad Spectrum SPF of 15 or higher and other sun protection measures including: ● Limit time in the sun, especially from 10 a.m.-2 p.m. ● Wear long-sleeve shirts, pants, hats, and sunglasses.

INACTIVE INGREDIENT

Alcohol, Isopropyl Myristate, Butyloctyl Salicylate, Acrylates/Octylacrylamide Copolymer, Water, Benzyl Glycol, Ethylhexylglycerin, 1,2-Hexanediol, Glycerin, Butylene Glycol, Sodium Hyaluronate, Ethyl Hexanediol, Centella Asiatica Extract, Madecassic Acid, Asiaticoside, Aslatic Acid, Hydrolyzed Hyaluronic Acid, Sodium Acetylated Hyaluronate, Fragrance

WARNINGS

●Danger : Flammable. Contents under pressure. Do not use near fire, heat or while smoking. Do not puncture or incinerate. Store at temperature below 120ºF(48ºC). Use only as directed. Intentional misuse by deliberately concentrating and inhaling the contents can be harmful or fatal.